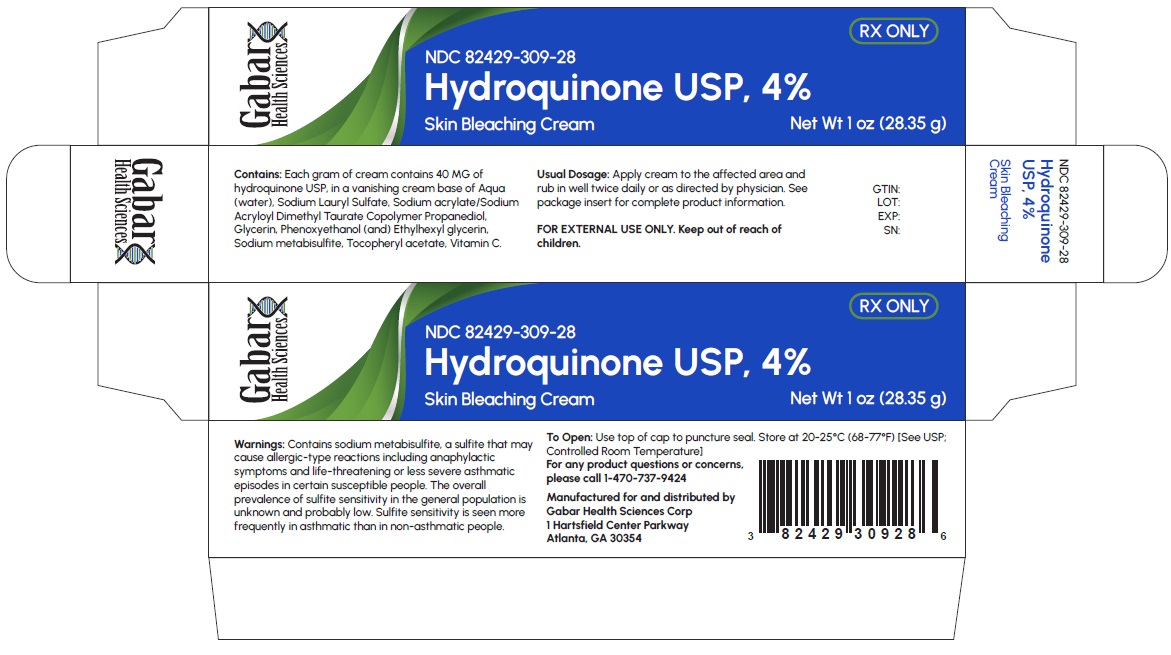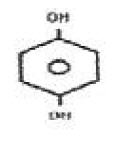 DRUG LABEL: Hydroquinone 4%
NDC: 82429-309 | Form: CREAM
Manufacturer: Gabar Health Sciences Corp.
Category: prescription | Type: HUMAN PRESCRIPTION DRUG LABEL
Date: 20231021

ACTIVE INGREDIENTS: HYDROQUINONE 40 mg/1 g
INACTIVE INGREDIENTS: WATER; SODIUM LAURYL SULFATE; SODIUM ACRYLATE/SODIUM ACRYLOYLDIMETHYLTAURATE COPOLYMER (4000000 MW); PROPANEDIOL; GLYCERIN; PHENOXYETHANOL; ETHYLHEXYLGLYCERIN; SODIUM METABISULFITE; .ALPHA.-TOCOPHEROL ACETATE; ASCORBIC ACID

Hydroquinone USP, 4%

Skin Bleaching Cream

Rx only

FOR EXTERNAL USE ONLY

NOT FOR OPHTHALMIC USE

DESCRIPTION

Each gram of Hydroquinone USP, 4% Skin Bleaching Cream contains 40 mg hydroquinone USP, in a vanishing cream base of Aqua (water), Sodium Lauryl Sulfate, Sodium acrylate/Sodium Acryloyl Dimethyl Taurate Copolymer, Propanediol, Glycerin, Phenoxyethanol (and) Ethylhexyl glycerin, Sodium metabisulfite, Tocopheryl acetate, Vitamin C. Chemically, hydroquinone is C6H6O2and has a molecular weight of 110.11. The chemical name is 1,4 dihydroxybenzene, and the structural formula of hydroquinone is:

CLINICAL PHARMACOLOGY

Topical application of hydroquinone produces a reversible depigmentation of the skin by inhibition of the enzymatic oxidation of tyrosine to 3,4-dihydroxyphenylalanine (dopa) (Denton, C. et al., 1952)^1and suppression of other melanocyte metabolic processes (Jimbow, K. et al., 1974)^2. Exposure to sunlight or ultraviolet light will cause repigmentation of bleached areas (Parrish, J.A. et al., 1978)^3.

INDICATIONS AND USAGE

Hydroquinone USP, 4% Skin Bleaching Cream is indicated for the gradual bleaching of hyperpigmented skin conditions such as chloasma, melasma, freckles, senile lentigines, and other unwanted areas of melanin hyperpigmentation.

CONTRAINDICATIONS

Prior history of sensitivity or allergic reaction to hydroquinone or to any of the ingredients of the product. The safety of topical hydroquinone use during pregnancy or for children (12 years and under) has not been established.

WARNINGS

Contains sodium metabisulfite, a sulfite that may cause allergic-type reactions, including anaphylactic symptoms and life-threatening or less severe asthmatic episodes in certain susceptible people. The overall prevalence of sulfite sensitivity in the general population is unknown and probably low. Sulfite sensitivity is seen more frequently in asthmatic than in non-asthmatic people. Since this product contains no sunscreen, an effective broad spectrum sun-blocking agent should be used and unnecessary solar exposure avoided, or protective clothing should be worn to cover bleached skin in order to prevent repigmentation from occurring. Hydroquinone may produce exogenous ochronosis, a gradual blue-black darkening of the skin. If this condition occurs, discontinue treatment and consult your physician. The majority of patients developing this condition are Black, but it may also occur in Caucasians and Hispanics.

PRECAUTIONS (see WARNINGS)

General

Test for skin sensitivity before using by applying a small amount to an unbroken patch of skin; check within 24 hours. Minor redness is not a contraindication, but where there is itching or vesicle formation or excessive inflammatory response further treatment ls not advised. Close patient supervision is recommended. Hydroquinone is a skin bleaching agent which may produce unwanted cosmetic effects if not used as directed. The physician should be familiar with the contents of this insert before prescribing or dispensing this medication.

Information for Patients

Sunscreen use is an essential aspect of hydroquinone therapy because even minimal sunlight sustains melanocytic activity. To prevent repigmentation, during treatment and maintenance therapy, sun exposure on treated skin should be avoided by application of a broad spectrum sunscreen (SPF 15 or greater) or by use of protective clothing.

Avoid contact with eyes and mucous membranes.

Keep this and all medications out of reach of children. In case of accidental ingestion, call a physician or a poison control center immediately.

Carcinogenesis, Mutagenesis, Impairment of Fertility

Studies of hydroquinone in animals have demonstrated some evidence of carcinogenicity. The carcinogenic potential of hydroquinone in humans is unknown. Published studies have demonstrated that hydroquinone is a mutagen and a clastogen. Treatment with hydroquinone has resulted in positive findings for genetic toxicity in the Ames assay in bacterial strains sensitive to oxidizing mutagens, in in vitrostudies in mammalian cells, and in the in vivomouse micronucleus assay.

Pregnancy

Teratogenic Effects

Pregnancy Category C

Animal reproduction studies have not been conducted with topical hydroquinone. It is also not known whether topical hydroquinone can cause fetal harm when administered to a pregnant woman or can affect reproduction capacity. Topical hydroquinone should be given to a pregnant woman only if clearly needed.

Nursing Mothers

It is not known whether this drug is excreted in human milk. Because many drugs are excreted in human milk, caution should be exercised when topical hydroquinone is administered to a nursing woman.

Pediatric Use

Safety and effectiveness for pediatric patients below the age of 12 years have not been established.

ADVERSE REACTIONS

The following adverse reactions have been reported: dryness and fissuring of paranasal and intraorbital areas, erythema, and stinging. Occasional hypersensitivity (localized contact dermatitis) may develop. If this occurs, the medication should be discontinued and the physician notified immediately.

OVERDOSAGE

There have been no systemic reactions reported from the use of topical hydroquinone. However, treatment should be limited to relatively small areas of the body at one time, since some patients experience a transient skin reddening and a mild burning sensation which does not preclude treatment.

DOSAGE AND ADMINISTRATION

Hydroquinone USP, 4% Skin Bleaching Cream should be applied to affected areas and rubbed in well twice daily, in the morning and before bedtime, or as directed by a physician. If no improvement is seen after 2 months of treatment, use of this product should be discontinued. There is no recommended dosage for pediatric patients under 12 years of age except under the advice and supervision of a physician.

HOW SUPPLIED

Hydroquinone USP, 4% Skin Bleaching Cream is available as follows:
1 oz (28.35 g) lube (NDC 82429-309-28)

STORAGE AND HANDLING

Store at 20-25°C (68-77°F) [see USP Controlled Room Temperature].

REFERENCES

1. DENTON C., LERNER A.B., FlTZPATRlCK T.B.
Inhibition of Melanin Formation by Chemical Agents
Journal of investigative Dermatology 1952, 18:119-135.

2. JIMBOW K. OBATA H., PATHAK M., FITZPATRICK T.B.
Mechanism of Depigmentation by Hydroquinone
Journal of Investigative Dermatology 1974, 62-136-449.

3. PARRISH J.A., ANDERSON R.R., URBACH F., PITTS D
UVA, Biological Effects of Ultraviolet Radiation with Emphasis on Human Responses to Longwave Ultraviolet Plenum Press, New York and London, 1978, p. 151

Manufactured for and distributed by:
Gabar Health Sciences Corp.
1 Hartsfield Center Parkway., Atlanta, GA 30354
Rev. 10/2023

PRINCIPAL DISPLAY PANEL - 28.35 g Tube Carton

Rx only

Gabar Health Sciences Corp.

NDC 82429-309-28

Hydroquinone USP, 4%

Skin Bleaching Cream

Net Wt 1 oz (28.35 g)